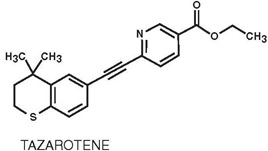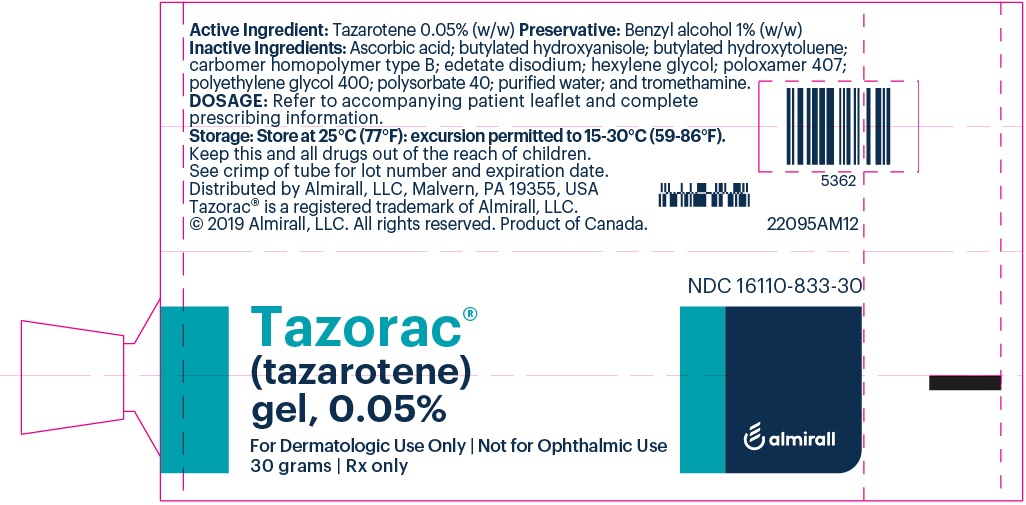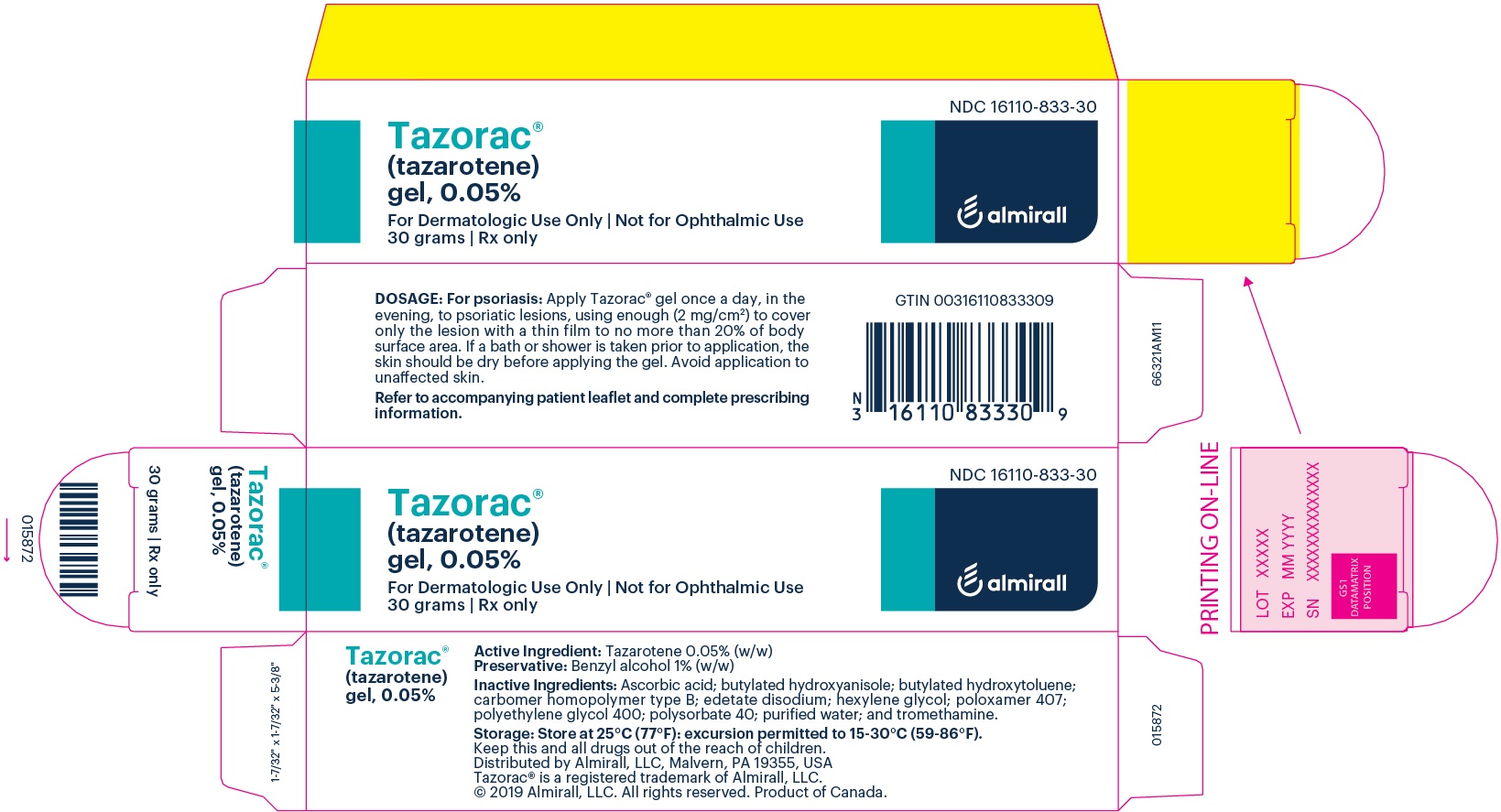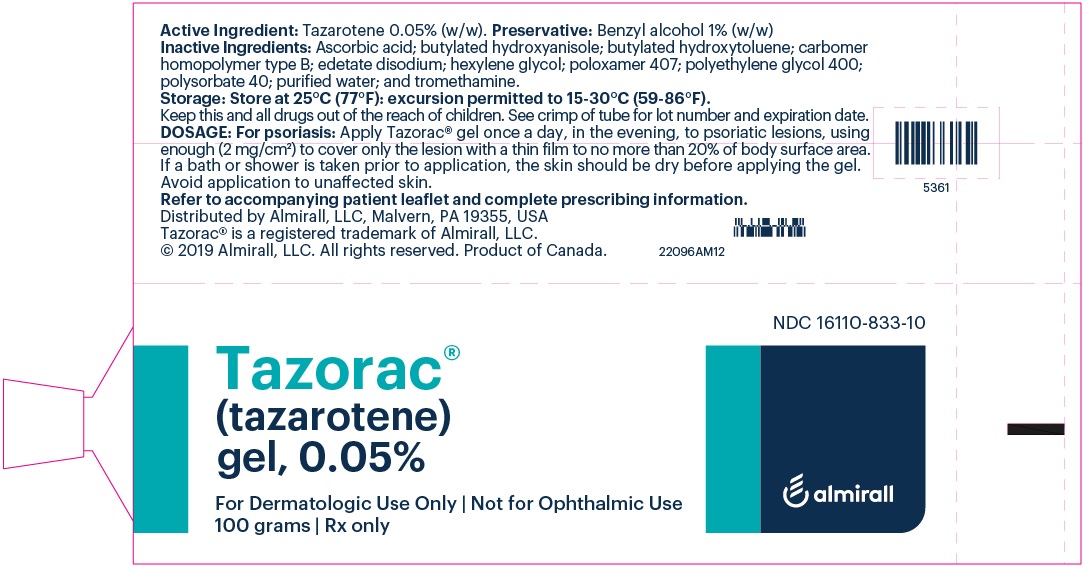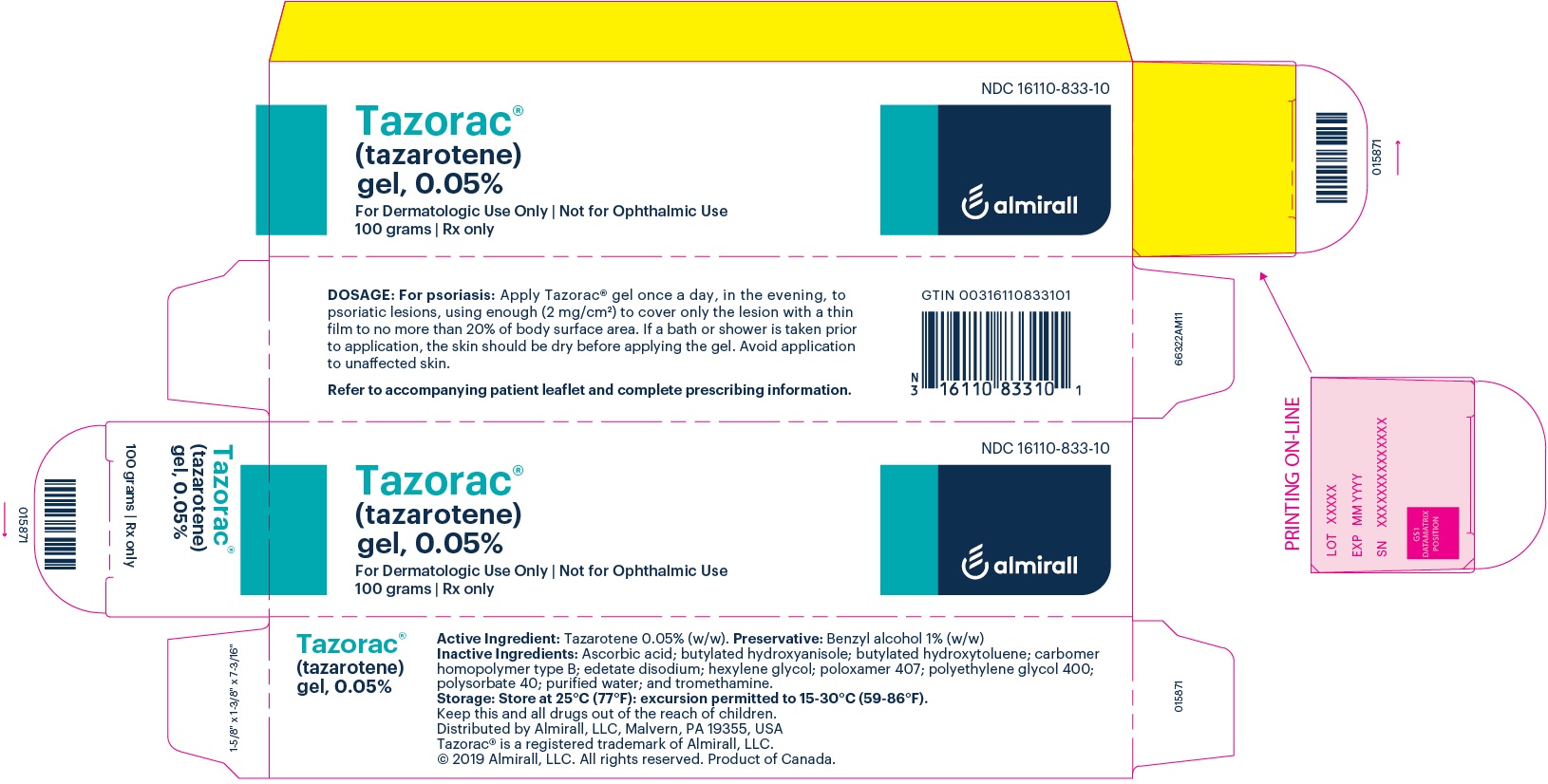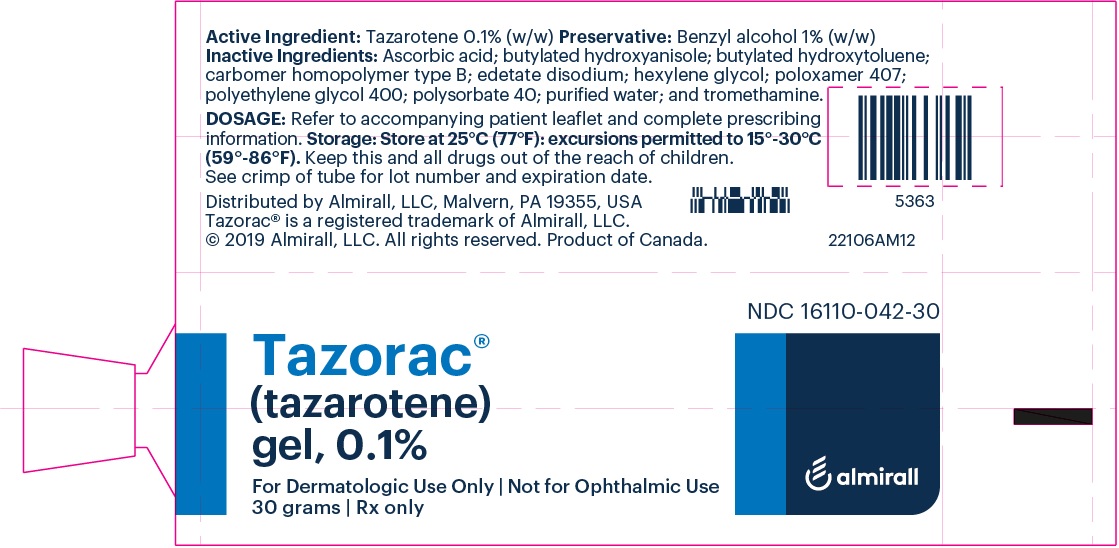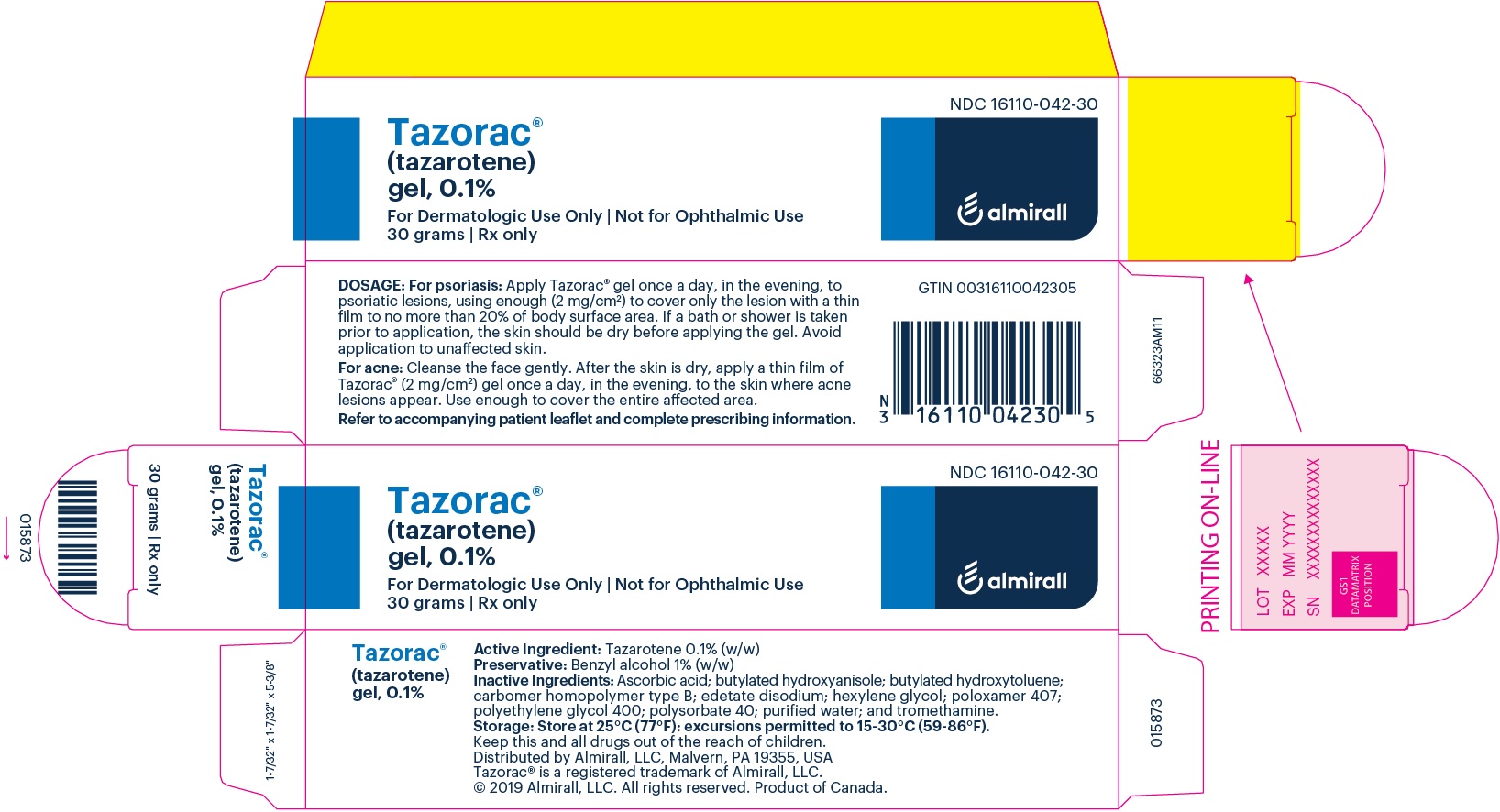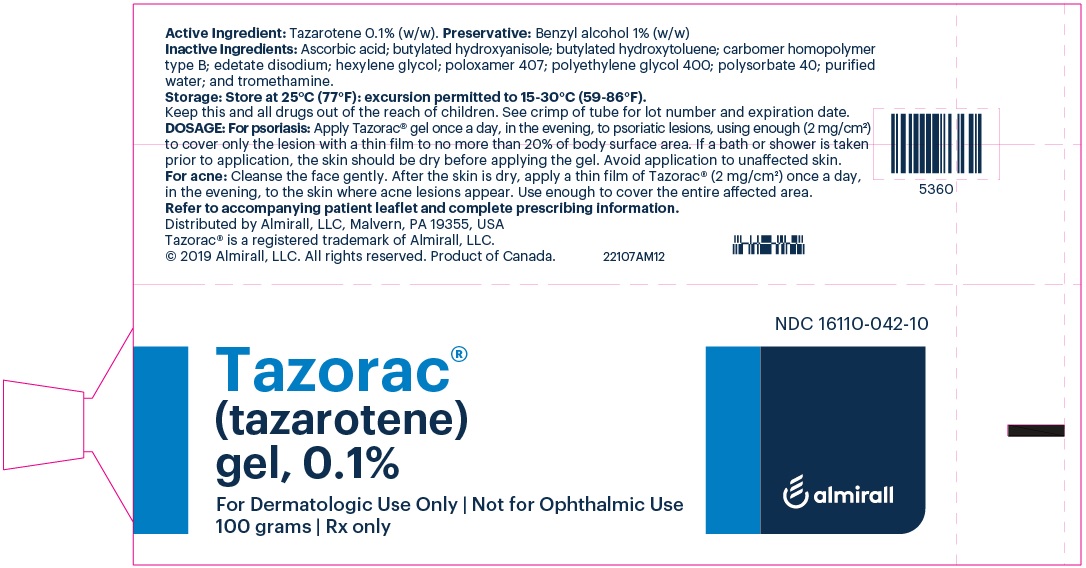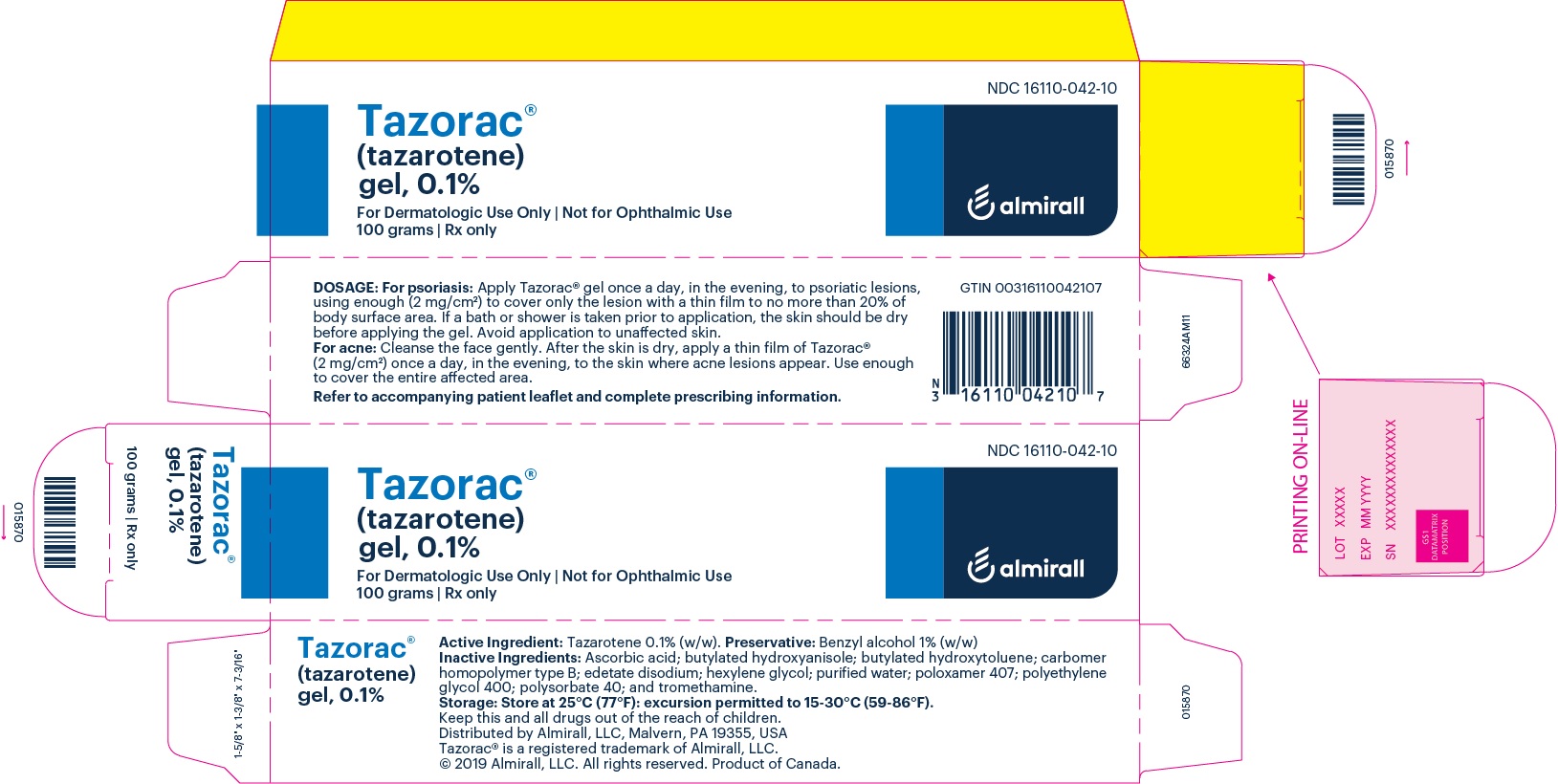 DRUG LABEL: Tazorac
NDC: 16110-833 | Form: GEL
Manufacturer: Almirall, LLC
Category: prescription | Type: HUMAN PRESCRIPTION DRUG LABEL
Date: 20251113

ACTIVE INGREDIENTS: TAZAROTENE 0.5 mg/1 g
INACTIVE INGREDIENTS: BENZYL ALCOHOL; ASCORBIC ACID; BUTYLATED HYDROXYANISOLE; BUTYLATED HYDROXYTOLUENE; CARBOMER HOMOPOLYMER TYPE B (ALLYL PENTAERYTHRITOL CROSSLINKED); EDETATE DISODIUM; HEXYLENE GLYCOL; POLOXAMER 407; POLYETHYLENE GLYCOL 400; POLYSORBATE 40; WATER; TROMETHAMINE

HIGHLIGHTS OF PRESCRIBING INFORMATION

These highlights do not include all the information needed to use TAZORAC® Gel safely and effectively. See full prescribing information for TAZORAC® Gel.
TAZORAC® (tazarotene) gel, 0.05% and 0.1%, for topical use
Initial U.S. Approval: 1997

1 INDICATIONS AND USAGE

- TAZORAC® Gel, 0.05% and 0.1% is a retinoid indicated for the topical treatment of plaque psoriasis of up to 20% body surface area involvement. (1.1)
- TAZORAC Gel, 0.1% is indicated for the topical treatment of mild to moderate facial acne vulgaris. (1.2)

Limitations of Use

- The safety of TAZORAC Gel use on more than 20% body surface area has not been established. (1.3)

2 DOSAGE AND ADMINISTRATION

- Apply a thin layer of TAZORAC Gel only to the affected area once daily in the evening. (2.1, 2.2)
- Not for ophthalmic, oral, or intravaginal use. (2.2)
- If contact with eyes occurs, rinse thoroughly with water. (2.2)

3 DOSAGE FORMS AND STRENGTHS

Gel, 0.05% and 0.1% (3)

4 CONTRAINDICATIONS

- Pregnancy (4, 8.1)
- Hypersensitivity (4)

5 WARNINGS AND PRECAUTIONS

- Embryofetal Toxicity: TAZORAC Gel contains tazarotene, which is a teratogen. TAZORAC Gel is contraindicated in pregnancy. Females of child-bearing potential should have a negative pregnancy test within 2 weeks prior to initiating treatment and use an effective method of contraception during treatment. (5.1)
- Local Irritation: Excessive pruritus, burning, skin redness or peeling can occur. If these reactions occur, discontinue until the integrity of the skin has been restored, or consider reducing dosing frequency or in the case of psoriasis, consider switching to the lower concentration. TAZORAC Gel should not be used on eczematous skin, as it may cause severe irritation. (5.2)
- Photosensitivity and Risk for Sunburn: Avoid exposure to sunlight, sunlamps, and weather extremes. Wear sunscreen daily. TAZORAC Gel should be administered with caution if the patient is also taking drugs known to be photosensitizers. (5.3)

6 ADVERSE REACTIONS

- Plaque Psoriasis: Most common adverse reactions occurring in 10 to 30% of patients are pruritus, burning/stinging, erythema, worsening of psoriasis, irritation, and skin pain. (6.1)
- Acne Vulgaris: Most common adverse reactions occurring in 10 to 30% of patients are desquamation, burning/stinging, dry skin, erythema and pruritus. (6.1)

To report SUSPECTED ADVERSE REACTIONS, contact Allergan, Inc. at 1-800-678-1605 or FDA at 1-800-FDA-1088 or www.fda.gov/medwatch.

FULL PRESCRIBING INFORMATION

1 INDICATIONS AND USAGE

1.1 Plaque Psoriasis

TAZORAC® (tazarotene) Gel, 0.05% and 0.1% are indicated for the topical treatment of patients with plaque psoriasis of up to 20% body surface area involvement.

1.2 Acne Vulgaris

TAZORAC (tazarotene) Gel, 0.1% is also indicated for the topical treatment of patients with facial acne vulgaris of mild to moderate severity.

The efficacy of TAZORAC Gel in the treatment of acne previously treated with other retinoids or resistant to oral antibiotics has not been established.

1.3 Limitations of Use

The safety of TAZORAC Gel use on more than 20% body surface area has not been established in psoriasis or acne [see Warnings and Precautions (5.1) and Use in Specific Populations (8.1)].

2 DOSAGE AND ADMINISTRATION

TAZORAC Gel is for topical use only. TAZORAC Gel is not for ophthalmic, oral, or intravaginal use. Avoid accidental transfer of TAZORAC Gel into eyes, mouth, or other mucous membranes. If contact with mucous membranes occurs, rinse thoroughly with water [see Warnings and Precautions (5.2)].

Wash hands thoroughly after application.

2.1 Psoriasis

It is recommended that treatment starts with TAZORAC Gel, 0.05%, with strength increased to 0.1% if tolerated and medically indicated. Apply a thin film (2 mg/cm^2) of TAZORAC Gel once per day, in the evening, to cover only the psoriatic lesions on no more than 20% of body surface area. If a bath or shower is taken prior to application, the skin should be dry before applying the gel. If emollients are used, they should be applied at least an hour before application of TAZORAC Gel. Because unaffected skin may be more susceptible to irritation, application of tazarotene to these areas should be carefully avoided. TAZORAC Gel was investigated for up to 12 months during clinical trials for psoriasis.

2.2 Acne

Cleanse the face gently. After the skin is dry, apply a thin layer (2 mg/cm^2) of TAZORAC Gel 0.1% once per day, in the evening, to the skin where acne lesions appear. Use enough to cover the entire affected area. TAZORAC Gel was investigated for up to 12 weeks during clinical trials for acne.

Use effective sunscreens and wear protective clothing while using TAZORAC Gel [see Warnings and Precautions (5.3)].

3 DOSAGE FORMS AND STRENGTHS

Gel, 0.05% and 0.1%, in 30 g and 100 g tubes. Each gram of TAZORAC Gel, 0.05% and 0.1% contains 0.5 mg and 1 mg of tazarotene, respectively in a translucent, aqueous gel.

4 CONTRAINDICATIONS

TAZORAC Gel is contraindicated in:

- Pregnancy. Retinoids may cause fetal harm when administered to a pregnant female [see Warnings and Precautions (5.1), Use in Specific Populations (8.1, 8.3)].
- Individuals who have known hypersensitivity to any of its components [see Warnings and Precautions (5.2)].

5 WARNINGS AND PRECAUTIONS

5.1 Embryofetal Toxicity

Based on data from animal reproduction studies, retinoid pharmacology and the potential for systemic absorption, TAZORAC Gel may cause fetal harm when administered to a pregnant female and is contraindicated during pregnancy. Tazarotene elicits malformations and developmental effects associated with retinoids after topical and oral administration to pregnant rats and rabbits during organogenesis.

Systemic exposure to tazarotenic acid is dependent upon the extent of the body surface area treated. In patients treated topically over sufficient body surface area, exposure could be in the same order of magnitude as in orally treated animals.

Although there may be less systemic exposure in the treatment of acne of the face alone due to less surface area for application, tazarotene is a teratogenic substance and causes fetal malformations in animals, and it is not known what level of exposure is required for teratogenicity in humans [see Clinical Pharmacology (12.3)].

There were thirteen reported pregnancies in subjects who participated in the clinical trials for topical tazarotene. Nine of the subjects had been treated with topical tazarotene, and the other four had been treated with vehicle. One of the subjects who was treated with tazarotene cream elected to terminate the pregnancy for non-medical reasons unrelated to treatment. The other eight pregnant women who were inadvertently exposed to topical tazarotene during the clinical trials subsequently delivered apparently healthy babies. As the exact timing and extent of exposure in relation to the gestation times are not certain, the significance of these findings is unknown.

Females of Child-bearing Potential

Females of child-bearing potential should be warned of the potential risk and use adequate birth-control measures when TAZORAC Gel is used. The possibility that a female of child-bearing potential is pregnant at the time of institution of therapy should be considered.

A negative result for pregnancy test should be obtained within 2 weeks prior to TAZORAC Gel therapy. TAZORAC Gel therapy should begin during a normal menstrual period [see Use in Specific Populations (8.1)].

5.2 Local Irritation and Hypersensitivity Reactions

Application of TAZORAC Gel may cause excessive irritation in the skin of certain sensitive individuals. Local reactions (including blistering and skin desquamation, pruritus, burning, erythema) and hypersensitivity adverse reactions (including urticaria) have been observed with topical tazarotene.

If these adverse reactions occur, consider discontinuing the medication or reducing the dosing frequency, as appropriate, until the integrity of the skin is restored. Alternatively, patients with psoriasis who are being treated with the 0.1% concentration can be switched to the lower concentration. Frequency of application should be closely monitored by careful observation of the clinical therapeutic response and skin tolerance. Therapy can be resumed, or the drug concentration or frequency of application can be increased as the patient becomes able to tolerate treatment.

Concomitant topical medications and cosmetics that have a strong drying effect should be avoided. It is also advisable to "rest" a patient's skin until the effects of such preparations subside before treatment with TAZORAC Gel is initiated.

TAZORAC Gel, should not be used on eczematous skin, as it may cause severe irritation.

Weather extremes, such as wind or cold, may be more irritating to patients using TAZORAC Gel.

5.3 Photosensitivity and Risk for Sunburn

Because of heightened burning susceptibility, exposure to sunlight (including sunlamps) should be avoided unless deemed medically necessary, and in such cases, exposure should be minimized during the use of TAZORAC Gel. Patients must be warned to use sunscreens and protective clothing when using TAZORAC Gel. Patients with sunburn should be advised not to use TAZORAC Gel until fully recovered. Patients who may have considerable sun exposure due to their occupation and those patients with inherent sensitivity to sunlight should exercise particular caution when using TAZORAC Gel.

TAZORAC Gel should be administered with caution if the patient is also taking drugs known to be photosensitizers (e.g., thiazides, tetracyclines, fluoroquinolones, phenothiazines, sulfonamides) because of the increased possibility of augmented photosensitivity.

6 ADVERSE REACTIONS

The following serious adverse reactions are discussed in more detail in other sections of the labeling:

• Embryofetal toxicity [see Warnings and Precautions (5.1)]

• Photosensitivity and Risk of Sunburn [see Warnings and Precautions (5.3)]

6.1 Clinical Trials Experience

Because clinical trials are conducted under widely varying conditions, adverse reaction rates observed in the clinical trials of a drug cannot be directly compared to rates in the clinical trials of another drug and may not reflect the rates observed in clinical practice.

Psoriasis

A total of 439 subjects 14 to 87 years of age were treated with TAZORAC Gel, 0.05% and 0.1% in two controlled clinical trials. The most frequent adverse events reported with TAZORAC Gel, 0.05% and 0.1% occurring in 10 to 30% of subjects, in descending order, included pruritus, burning/stinging, erythema, worsening of psoriasis, irritation, and skin pain. Reactions occurring in 1 to 10% of subjects included rash, desquamation, irritant contact dermatitis, skin inflammation, fissuring, bleeding, and dry skin. Increases in “psoriasis worsening” and “sun-induced erythema” were noted in some subjects over the 4th to 12th months of treatment as compared to the first three months of a 1 year study. In general, the incidence of adverse events with TAZORAC Gel 0.05% was 2 to 5% lower than that seen with TAZORAC Gel 0.1%.

Acne

A total of 596 subjects 12 to 44 years of age were treated with TAZORAC Gel, 0.05% and 0.1% in two controlled clinical trials. The most frequent adverse events reported during clinical trials with TAZORAC Gel, 0.1% in the treatment of acne occurring in 10 to 30% of subjects, in descending order, included desquamation, burning/stinging, dry skin, erythema and pruritus. Reactions occurring in 1 to 10% of subjects included irritation, skin pain, fissuring, localized edema and skin discoloration.

6.2 Postmarketing Experience

Because these reactions are reported voluntarily from a population of uncertain size, it is not always possible to reliably estimate their frequency or establish a causal relationship to drug exposure. The following adverse reactions have been identified during postapproval use of tazarotene.

Skin and subcutaneous tissue disorders: blister, dermatitis, urticaria, skin exfoliation, skin discoloration (including skin hyperpigmentation or skin hypopigmentation), swelling at or near application sites, and pain.

7 DRUG INTERACTIONS

No formal drug-drug interaction studies were conducted with TAZORAC Gel.

In a trial of 27 healthy female subjects between the ages of 20–55 years receiving a combination oral contraceptive tablet containing 1 mg norethindrone and 35 mcg ethinyl estradiol, concomitant use of tazarotene administered as 1.1 mg orally (mean ± SD Cmax and AUC0-24 of tazarotenic acid were 28.9 ± 9.4 ng/mL and 120.6 ± 28.5 ng•hr/mL, respectively) did not affect the pharmacokinetics of norethindrone and ethinyl estradiol over a complete cycle.

The impact of tazarotene on the pharmacokinetics of progestin only oral contraceptives (i.e., minipills) has not been evaluated.

8 USE IN SPECIFIC POPULATIONS

8.1 Pregnancy

Risk Summary

Based on data from animal reproduction studies, retinoid pharmacology, and the potential for systemic absorption, TAZORAC Gel may cause fetal harm when administered to a pregnant female and is contraindicated during pregnancy. Safety in pregnant females has not been established. The potential risk to the fetus outweighs the potential benefit to the mother from TAZORAC Gel during pregnancy; therefore, TAZORAC Gel should be discontinued as soon as pregnancy is recognized [see Contraindications (4), Warnings and Precautions (5.1), Clinical Pharmacology (12.3)]. Limited case reports of pregnancy in females enrolled in clinical trials for TAZORAC Gel have not established a clear association with tazarotene and major birth defects or miscarriage risk. Because the exact timing and extent of exposure in relation to the gestational age are not certain, the significance of these findings is unknown.

In animal reproduction studies with pregnant rats, tazarotene dosed topically during organogenesis at 0.5 times the maximum systemic exposure in subjects treated with the maximum recommended human dose (MRHD) of tazarotene gel, 0.1% resulted in reduced fetal body weights and reduced skeletal ossification. In animal reproduction studies with pregnant rabbits dosed topically with tazarotene gel at 7 times the maximum systemic exposure in subjects treated with the MRHD of tazarotene gel, 0.1%, there were single incidences of known retinoid malformations, including spina bifida, hydrocephaly, and heart anomalies.

In animal reproduction studies with pregnant rats and rabbits, tazarotene dosed orally during organogenesis at 0.5 and 13 times, respectively, the maximum systemic exposure in subjects treated with the MRHD of tazarotene gel, 0.1% resulted in malformations, fetal toxicity, developmental delays, and/or behavioral delays. In pregnant rats, tazarotene dosed orally prior to mating through early gestation resulted in decreased litter size, decreased numbers of live fetuses, decreased fetal body weights, and increased malformations at doses approximately 2 times higher than the maximum systemic exposure in subjects treated with the MRHD of tazarotene gel, 0.1% [see Data].

The background risk of major birth defects and miscarriage for the indicated population is unknown. Adverse outcomes in pregnancy occur regardless of the health of the mother or the use of medications. In the U.S. general population, the estimated background risk of major birth defects and miscarriage in clinically recognized pregnancies is 2-4% and 15-20%, respectively.

Data

Animal Data

In rats, a tazarotene gel, 0.05% formulation dosed topically during gestation days 6 through 17 at 0.25 mg/kg/day, which represented 0.5 times the maximum systemic exposure in subjects treated with the MRHD of tazarotene gel, 0.1% (i.e., 2 mg/cm^2 over a 20% body surface area), resulted in reduced fetal body weights and reduced skeletal ossification. Rabbits dosed topically with 0.25 mg/kg/day tazarotene gel, which represented 7 times the maximum systemic exposure in subjects treated with the MRHD of tazarotene gel, 0.1%, during gestation days 6 through 18 were noted with single incidences of known retinoid malformations, including spina bifida, hydrocephaly, and heart anomalies.

When tazarotene was given orally to animals, developmental delays were seen in rats, and malformations and post-implantation loss were observed in rats and rabbits at doses producing 0.5 and 13 times, respectively, the maximum systemic exposure in subjects treated with the MRHD of tazarotene gel, 0.1%.

In female rats orally administered 2 mg/kg/day of tazarotene from 15 days before mating through gestation day 7, which represented 2 times the maximum systemic exposure in subjects treated with the MRHD of tazarotene gel, 0.1%, classic developmental effects of retinoids were observed including decreased number of implantation sites, decreased litter size, decreased numbers of live fetuses, and decreased fetal body weights. A low incidence of retinoid-related malformations was observed at that dose.

In a pre- and postnatal development toxicity study, topical administration of tazarotene gel (0.125 mg/kg/day) to pregnant female rats from gestation day 16 through lactation day 20 reduced pup survival, but did not affect the reproductive capacity of the offspring. Based on data from another study, the maximum systemic exposure in the rat would be 0.3 times the maximum systemic exposure in subjects treated with the MRHD of tazarotene gel, 0.1%.

8.2 Lactation

Risk Summary

There is no information regarding the presence of tazarotene in human milk, the effects on the breastfed infant, or the effects on milk production. After single topical doses of ^14C-tazarotene gel to the skin of lactating rats, radioactivity was detected in rat milk. The lack of clinical data during lactation precludes a clear determination of the risk of TAZORAC Gel to an infant during lactation; therefore, the developmental and health benefits of breastfeeding should be considered along with the mother’s clinical need for TAZORAC Gel and any potential adverse effects on the breastfed child from TAZORAC Gel or from the underlying maternal condition.

8.3 Females and Males of Reproductive Potential

Pregnancy Testing

Pregnancy testing is recommended for females of reproductive potential within 2 weeks prior to initiating TAZORAC Gel therapy which should begin during a menstrual period.

Contraception

Females

Based on animal studies, TAZORAC Gel may cause fetal harm when administered to a pregnant woman [see Use in Specific Populations (8.1)]. Advise females of reproductive potential to use effective contraception during treatment with TAZORAC Gel.

8.4 Pediatric Use

The safety and efficacy of TAZORAC Gel have not been established in pediatric patients with psoriasis or acne under the age of 12 years.

8.5 Geriatric Use

Of the total number of subjects in clinical trials of TAZORAC Gel for plaque psoriasis, 163 were over the age of 65. Subjects over 65 years of age experienced more adverse events and lower treatment success rates after 12 weeks of use of TAZORAC Gel compared with those 65 years of age and younger. Currently there is no other clinical experience on the differences in responses between the elderly and younger subjects, but greater sensitivity of some older individuals cannot be ruled out. Tazarotene gel for the treatment of acne has not been clinically evaluated in persons over the age of 65.

10 OVERDOSAGE

Excessive topical use of TAZORAC Gel, 0.05% and 0.1% may lead to marked redness, peeling, or discomfort [see Warnings and Precautions (5.2)].

TAZORAC Gel 0.05% and 0.1% are not for oral use. Oral ingestion of the drug may lead to the same adverse effects as those associated with excessive oral intake of Vitamin A (hypervitaminosis A) or other retinoids. If oral ingestion occurs, the patient should be monitored, and appropriate supportive measures should be administered as necessary.

11 DESCRIPTION

TAZORAC (tazarotene) Gel, 0.05% and 0.1% is for topical use and contains the active ingredient, tazarotene. Each gram of TAZORAC Gel, 0.05% and 0.1% contains 0.5 and 1 mg of tazarotene, respectively in a translucent, aqueous gel.

Tazarotene is a member of the acetylenic class of retinoids. Chemically, tazarotene is ethyl 6-[(4,4-dimethylthiochroman-6-yl)ethynyl]nicotinate. The compound has an empirical formula of C21H21NO2S and molecular weight of 351.46. The structural formula is shown below:

TAZORAC Gel contains the following inactive ingredients:

benzyl alcohol 1%;ascorbic acid; butylated hydroxyanisole; butylated hydroxytoluene; carbomer homopolymer type B; edetate disodium; hexylene glycol; poloxamer 407; polyethylene glycol 400; polysorbate 40; purified water; and tromethamine.

12 CLINICAL PHARMACOLOGY

12.1 Mechanism of Action

Tazarotene is a retinoid prodrug which is converted to its active form, the carboxylic acid of tazarotene, by deesterification. Tazarotenic acid binds to all three members of the retinoic acid receptor (RAR) family: RARα, RARβ, and RARγ, but shows relative selectivity for RARβ, and RARγ and may modify gene expression. The clinical significance of these findings for the treatment of plaque psoriasis and facial acne vulgaris is unknown.

12.2 Pharmacodynamics

The pharmacodynamics of TAZORAC Gel in the treatment of plaque psoriasis and facial acne vulgaris are unknown.

12.3 Pharmacokinetics

Following topical application, tazarotene undergoes esterase hydrolysis to form its active metabolite, tazarotenic acid. Little parent compound could be detected in the plasma. Tazarotenic acid was highly bound to plasma proteins (greater than 99%).

Tazarotene and tazarotenic acid were metabolized to sulfoxides, sulfones and other polar metabolites which were eliminated through urinary and fecal pathways. The half-life of tazarotenic acid was approximately 18 hours, following topical application of tazarotene to normal, acne or psoriatic skin.

The human in vivo studies described below were conducted with tazarotene gel applied topically at approximately 2 mg/cm^2 and left on the skin for 10 to 12 hours. Both the peak plasma concentration (Cmax) and area under the plasma concentration time curve (AUC) refer to the active metabolite only.

Two single, topical dose studies were conducted using ^14C-tazarotene gel. Systemic absorption, as determined from radioactivity in the excreta, was less than 1% of the applied dose (without occlusion) in six subjects with psoriasis and approximately 5% of the applied dose (under occlusion) in six healthy subjects. One non-radiolabeled single-dose study comparing the 0.05% gel to the 0.1% gel in healthy subjects indicated that the Cmax and AUC were 40% higher for the 0.1% gel.

After 7 days of topical dosing with measured doses of tazarotene 0.1% gel on 20% of the total body surface without occlusion in 24 healthy subjects, the Cmax for tazarotenic acid was 0.72 ± 0.58 ng/mL (mean ± SD) occurring 9 hours after the last dose, and the AUC0-24hr for tazarotenic acid was 10.1 ± 7.2 ng·hr/mL. Systemic absorption was 0.91 ± 0.67% of the applied dose.

In a 14-day study in five subjects with psoriasis, measured doses of tazarotene 0.1% gel were applied daily by nursing staff to involved skin without occlusion (8 to 18% of total body surface area; mean ± SD: 13 ± 5%). The Cmax for tazarotenic acid was 12.0 ± 7.6 ng/mL occurring 6 hours after the final dose, and the AUC0-24hr for tazarotenic acid was 105 ± 55 ng·hr/mL. Systemic absorption was 14.8 ± 7.6% of the applied dose. Extrapolation of these results to represent dosing on 20% of total body surface yielded estimates for tazarotenic acid with Cmax of 18.9 ± 10.6 ng/mL and AUC0-24hr of 172 ± 88 ng·hr/mL.

An in vitro percutaneous absorption study, using radiolabeled drug and freshly excised human skin or human cadaver skin, indicated that approximately 4 to 5% of the applied dose was in the stratum corneum (tazarotene: tazarotenic acid = 5:1) and 2 to 4% was in the viable epidermis-dermis layer (tazarotene: tazarotenic acid = 2:1) 24 hours after topical application of the gel.

13 NONCLINICAL TOXICOLOGY

13.1 Carcinogenesis, Mutagenesis, Impairment of Fertility

A long-term study of tazarotene following oral administration of 0.025, 0.050, and 0.125 mg/kg/day to rats showed no indications of increased carcinogenic risks. Based on pharmacokinetic data from a shorter-term study in rats, the highest dose of 0.125 mg/kg/day was anticipated to give systemic exposure in the rat 0.3 times that seen in subjects treated with the MRHD of tazarotene gel, 0.1%.

A long-term study with topical administration of up to 0.1% tazarotene in a gel formulation in mice terminated at 88 weeks showed that dose levels of 0.05, 0.125, 0.25, and 1 mg/kg/day (reduced to 0.5 mg/kg/day for males after 41 weeks due to severe dermal irritation) revealed no apparent carcinogenic effects when compared to vehicle control animals. Systemic exposure at the highest dose was 2 times that seen in subjects treated with the MRHD of tazarotene gel, 0.1%.

Tazarotene was non-mutagenic in the Ames assay and did not produce structural chromosomal aberrations in a human lymphocyte assay. Tazarotene was non-mutagenic in the CHO/HGPRT mammalian cell forward gene mutation assay and was non-clastogenic in the in vivo mouse micronucleus test.

No impairment of fertility occurred in rats when male animals were treated for 70 days prior to mating and female animals were treated for 14 days prior to mating and continuing through gestation and lactation with topical doses of tazarotene gel up to 0.125 mg/kg/day. Based on data from another study, the systemic drug exposure in the rat at the highest dose was 0.3 times that observed in subjects treated with the MRHD of tazarotene gel, 0.1%.

No impairment of mating performance or fertility was observed in male rats treated for 70 days prior to mating with oral doses of up to 1 mg/kg/day tazarotene, which produced systemic exposure that was approximately equivalent to that observed in subjects treated with the MRHD of tazarotene gel, 0.1%.

No impairment of mating performance or fertility was observed in female rats treated for 15 days prior to mating and continuing through gestation day 7 with oral doses of tazarotene up to 2 mg/kg/day. However, there was a significant decrease in the number of estrous stages and an increase in developmental effects at that dose, which produced systemic exposure 2 times that observed in subjects treated with the MRHD of tazarotene gel, 0.1% [see Use in Specific Populations (8.1)].

14 CLINICAL STUDIES

Psoriasis: In two large vehicle-controlled clinical trials, TAZORAC Gel, 0.05% and 0.1% applied once daily for 12 weeks was significantly more effective than vehicle in reducing the severity of the clinical signs of plaque psoriasis covering up to 20% of body surface area. In one of the studies, subjects were followed up for an additional 12 weeks following cessation of therapy with TAZORAC Gel. Mean baseline scores and changes from baseline (reductions) after treatment in these two trials are shown in Table 1.

Table 1. Plaque Elevation, Scaling, and Erythema in Two Controlled Clinical Trials for Psoriasis
 |  | TAZORAC® 0.05% Gel |  |  |  | TAZORAC® 0.1% Gel |  |  |  | Vehicle Gel
 |  | Trunk/Arm/Leg Lesions |  | Knee/Elbow Lesions |  | Trunk/Arm/Leg Lesions |  | Knee/Elbow Lesions |  | Trunk/Arm/Leg Lesions |  | Knee/Elbow Lesions
 |  | N=108 | N=111 | N=108 | N=111 | N=108 | N=112 | N=108 | N=112 | N=108 | N=113 | N=108 | N=113
Plaque Elevation | B* C-12* C-24* | 2.5 -1.4 -1.2 | 2.6 -1.3 | 2.6 -1.3 -1.1 | 2.6 -1.1 | 2.5 -1.4 -1.1 | 2.6 -1.4 | 2.6 -1.5 -1.0 | 2.6 -1.3 | 2.4 -0.8 -0.9 | 2.6 -0.7 | 2.6 -0.7 -0.7 | 2.6 -0.6
Scaling | B* C-12* C-24* | 2.4 -1.1 -0.9 | 2.5 -1.1 | 2.5 -1.1 -0.8 | 2.6 -0.9 | 2.4 -1.3 -1.0 | 2.6 -1.3 | 2.5 -1.2 -0.8 | 2.7 -1.2 | 2.4 -0.7 -0.8 | 2.6 -0.7 | 2.5 -0.6 -0.7 | 2.7 -0.6
Erythema | B* C-12* C-24* | 2.4 -1.0 -1.1 | 2.7 -0.8 | 2.2 -0.9 -0.7 | 2.5 -0.8 | 2.4 -1.0 -0.9 | 2.8 -1.1 | 2.3 -1.0 -0.8 | 2.5 -0.8 | 2.3 -0.6 -0.7 | 2.7 -0.5 | 2.2 -0.5 -0.6 | 2.5 -0.5
Plaque elevation, scaling, and erythema scored on a 0-4 scale with 0=none, 1=mild, 2=moderate, 3=severe and 4=very severe.
B*=Mean Baseline Severity: C-12*=Mean Change from Baseline at end of 12 weeks of therapy:
C-24*=Mean Change from Baseline at week 24 (12 weeks after the end of therapy).

Global improvement over baseline at the end of 12 weeks of treatment in these two trials is shown in Table 2.

Table 2. Global Improvement over Baseline after Twelve Weeks of Treatment in Two Controlled Clinical Trials for Psoriasis
 | TAZORAC® 0.05% Gel |  | TAZORAC® 0.1% Gel |  | Vehicle Gel
 | N=81 | N=93 | N=79 | N=69 | N=84 | N=91
100% improvement | 2 (2%) | 1 (1%) | 0 | 0 | 1 (1%) | 0
75% improvement | 23 (28%) | 17 (18%) | 30 (38%) | 17 (25%) | 10 (12%) | 9 (10%)
50% improvement | 42 (52%) | 39 (42%) | 51 (65%) | 36 (52%) | 28 (33%) | 21 (23%)
1-49% improvement | 21 (26%) | 32 (34%) | 18 (23%) | 23 (33%) | 27 (32%) | 32 (35%)
No change or worse | 18 (22%) | 22 (24%) | 10 (13%) | 10 (14%) | 29 (35%) | 38 (42%)

The 0.1% gel was more effective than the 0.05% gel, but the 0.05% gel was associated with less local irritation than the 0.1% gel [see Adverse Reactions (6.1)].

Acne: In two large vehicle-controlled trials, TAZORAC Gel, 0.1% applied once daily was significantly more effective than vehicle in the treatment of facial acne vulgaris of mild to moderate severity. Percent reductions in lesion counts after treatment for 12 weeks in these two trials are shown in Table 3.

Table 3. Reduction in Lesion Counts after Twelve Weeks of Treatment in Two Controlled Clinical Trials for Acne
 | TAZORAC® 0.1% Gel |  | Vehicle Gel
 | N=150 | N=149 | N=148 | N=149
Noninflammatory lesions | 55% | 43% | 35% | 27%
Inflammatory lesions | 42% | 47% | 30% | 28%
Total lesions | 52% | 45% | 33% | 27%

Global improvement over baseline at the end of 12 weeks of treatment in these two trials is shown in Table 4.

Table 4. Global Improvement over Baseline after Twelve Weeks of Treatment in Two Controlled Clinical Trials for Acne
 | TAZORAC® 0.1% Gel |  | Vehicle Gel
 | N=105 | N=117 | N=117 | N=110
100% improvement | 1 (1%) | 0 | 0 | 0
75% improvement | 40 (38%) | 21 (18%) | 23 (20%) | 11 (10%)
50% improvement | 71 (68%) | 56 (48%) | 47 (40%) | 32 (29%)
1-49% improvement | 23 (22%) | 49 (42%) | 48 (41%) | 46 (42%)
No change or worse | 11 (10%) | 12 (10%) | 22 (19%) | 32 (29%)

16 HOW SUPPLIED/STORAGE AND HANDLING

TAZORAC (tazarotene) Gel is a translucent, aqueous gel, available in concentrations of 0.05% and 0.1%. It is available in a collapsible aluminum tube with a tamper-evident aluminum membrane over the opening and a white propylene screw cap, in 30 g and 100 g sizes.

TAZORAC Gel 0.05% 30 g NDC 16110-833-30
TAZORAC Gel 0.05% 100 g NDC 16110-833-10
TAZORAC Gel 0.1% 30 g NDC 16110-042-30
TAZORAC Gel 0.1% 100 g NDC 16110-042-10

Storage: Store at 20°C to 25°C (68°F to 77°F). Excursions permitted from 15°C to 30°C (59°F to 86°F).

17 PATIENT COUNSELING INFORMATION

Advise the patient to read the FDA-approved patient labeling (Patient Information).

Embryofetal Toxicity

Inform females of reproductive potential of the potential risk to a fetus. Advise these patients to use effective contraception during treatment with TAZORAC Gel. Advise patients to inform their healthcare provider of a known or suspected pregnancy [see Warnings and Precautions (5.1) and Use in Specific Populations (8.1, 8.3)].

Photosensitivity and Risk of Sunburn

Advise patients to avoid excessive sun exposure and to use of sunscreens and protective measures (hat, visor). Advise patients to avoid using TAZORAC Gel if also taking other medicines may increase sensitivity to sunlight.

Important Administration Instructions

Advise the patient of the following:

1. For the patient with psoriasis, apply TAZORAC Gel only to psoriasis skin lesions, avoiding uninvolved skin.
2. If undue irritation (redness, peeling, or discomfort) occurs, reduce frequency of application or temporarily interrupt treatment. Treatment may be resumed once irritation subsides [see Dosage and Adminstration (2.1)].
3. Moisturizers may be used as frequently as desired.
4. Patients with psoriasis may use a cream or lotion to soften or moisten skin at least 1 hour before applying TAZORAC Gel.
5. Avoid contact with the eyes. If TAZORAC Gel gets in or near eyes, rinse thoroughly with water. Seek medical attention if eye irritation continues.
6. TAZORAC Gel is for topical use only. Do not apply to eyes, mouth, or other mucous membrane. Not for ophthalmic, oral, or intravaginal use.
7. Wash hands thoroughly after applying TAZORAC Gel.

Revised: 08/2019

Distributed by: Almirall, LLC
Exton, PA 19341

© 2019 Almirall, Inc. All rights reserved.
All trademarks are the property of their respective owners.

71722AM11

Pharmacist: Please cut or tear at dotted line and provide this patient package insert to your customer.

PATIENT INFORMATION
TAZORAC® (TAZ-or-ac)
(tazarotene)
Gel, 0.05% and 0.1%

Important information: TAZORAC Gel is for use on skin only. Do not use TAZORAC Gel in your eyes, mouth, or vagina.

What is the most important information I should know about TAZORAC Gel?
TAZORAC Gel may cause birth defects if used during pregnancy.

- Females must not be pregnant when they start using TAZORAC Gel or become pregnant during treatment with TAZORAC Gel.
- For females who can become pregnant:
  - Your doctor will order a pregnancy test for you within 2 weeks before you begin treatment with TAZORAC Gel to be sure that you are not pregnant. Your doctor will decide when to do the test.
  - Begin treatment with TAZORAC Gel during a normal menstrual period.
  - Use an effective form of birth control during treatment with TAZORAC Gel. Talk with your doctor about birth control options that may be used to prevent pregnancy during treatment with TAZORAC Gel.
  - Stop using TAZORAC Gel and tell your doctor right away if you become pregnant while using TAZORAC Gel.

What is TAZORAC Gel?

- TAZORAC Gel 0.05% and 0.1% is a prescription medicine used on the skin (topical) to treat people with stable plaque psoriasis on up to 20% of your body surface.
- TAZORAC Gel 0.1% is also used on the skin to treat people with mild to moderate facial acne vulgaris.

It is not known if TAZORAC Gel is:

- safe and effective for use in children under 12 years of age.
- effective for the treatment of acne in people who have been treated with retinoid medicines or have acne that does not respond to treatment with oral antibiotics.
- safe if used over more than 20% of your body for the treatment of psoriasis or acne.

Who should not use TAZORAC Gel?
Do not use TAZORAC Gel if you:

- are pregnant or plan to become pregnant. See “What is the most important information I should know about TAZORAC Gel?” at the beginning of this leaflet.
- are allergic to tazarotene or any of the ingredients in TAZORAC Gel. See the end of this leaflet for a complete list of ingredients in TAZORAC Gel.

What should I tell my doctor before using TAZORAC Gel?
Before you use TAZORAC Gel, tell your doctor about all of your medical conditions, including if you:

- have eczema or any other skin problems
- are breastfeeding or plan to breastfeed. It is not known if TAZORAC Gel passes into your breast milk. Talk to your doctor about using TAZORAC Gel while breastfeeding.

Tell your doctor about all the medicines you take, including prescription and over-the-counter medicines, vitamins, and herbal supplements.
Certain medicines, vitamins, or supplements may make your skin more sensitive to sunlight.
Also, tell your doctor about any cosmetics you use, including moisturizers, creams, lotions, or products that can dry out your skin.
Keep a list of your medicines to show to your doctor and pharmacist when you get a new medicine.

How should I use TAZORAC Gel?

- Use TAZORAC Gel exactly as your doctor tells you to use it.
- Apply TAZORAC Gel 1 time each day, in the evening.
- Do not get TAZORAC Gel in your eyes, on your eyelids, or in your mouth. If TAZORAC Gel gets in or near your eyes, rinse them well with water. Call your doctor or get medical help if you have eye irritation that does not go away.
- Wash your hands after applying TAZORAC Gel.

Follow these instructions for applying TAZORAC Gel:

- If you have psoriasis:
  ○ If you shower or bathe before applying TAZORAC Gel, your skin should be dry before applying the gel.
  ○ You may use a cream or lotion to soften or moisten your skin at least 1 hour before you apply TAZORAC Gel.
  ○ Apply a thin layer of TAZORAC Gel to cover only the psoriasis lesions.
- If you have acne:
  ○ Gently wash and dry your face before applying TAZORAC Gel.
  ○ Apply a thin layer of TAZORAC Gel to cover only the acne lesions.
- If you swallow TAZORAC Gel, call your doctor or go to the nearest hospital emergency room right away.

What should I avoid while using TAZORAC Gel?

- Avoid sunlight, including sunlamps, during treatment with TAZORAC Gel. TAZORAC Gel can make you more sensitive to the sun, and the light from sunlamps and tanning beds. You could get a severe sunburn. Use sunscreen and wear a hat and clothes that cover your skin if you have to be in sunlight.
- Talk to your doctor if you get a sunburn during treatment with TAZORAC Gel. If you get a sunburn, do not use TAZORAC Gel until your sunburn is healed.
- Avoid using cosmetics or topical medicines that may make your skin more sensitive to sunlight or make your skin dry.
- Avoid using TAZORAC Gel on unaffected skin or skin with eczema because it may cause severe irritation.

What are the possible side effects of TAZORAC Gel?
TAZORAC Gel may cause serious side effects, including:

- Skin irritation and allergic reactions (hypersensitivity). TAZORAC Gel may cause increased skin irritation (including blistering and skin peeling) and allergic reactions (including hives). Tell your doctor if you develop itching, burning, redness, blistering or peeling of your skin during treatment with TAZORAC Gel. If you develop skin irritation or hives, your doctor may tell you to temporarily stop using TAZORAC Gel until your skin heals, tell you to use TAZORAC Gel less often, or change your TAZORAC Gel dose. Also, wind or cold weather may be more irritating to your skin while you are using TAZORAC Gel.
- Sensitivity to sunlight and risk of sunburn. See “What should I avoid while using TAZORAC Gel?”

The most common side effects of TAZORAC Gel in people with plaque psoriasis include itching, burning, redness, worsening of psoriasis, irritation and skin pain.
The most common side effects of TAZORAC Gel in people with acne include peeling, burning, dry skin, redness and itching.
These are not all the possible side effects of TAZORAC Gel. Call your doctor for medical advice about side effects. You may report side effects to FDA at 1-800-FDA-1088.

How should I store TAZORAC Gel?

- Store TAZORAC Gel at 68°F to 77°F (20°C to 25°C).
- Keep TAZORAC Gel and all medicines out of the reach of children.

General information about the safe and effective use of TAZORAC Gel.
Medicines are sometimes prescribed for purposes other than those listed in a Patient Information leaflet. Do not use TAZORAC Gel for a condition for which it was not prescribed. Do not give TAZORAC Gel to other people, even if they have the same symptoms you have. It may harm them. You can ask your doctor or pharmacist for information about TAZORAC Gel that is written for health professionals.

What are the ingredients in TAZORAC Gel?
Active ingredient: tazarotene
Inactive ingredients: ascorbic acid, benzyl alcohol, butylated hydroxyanisole, butylated hydroxytoluene, carbomer homopolymer type B, edetate disodium, hexylene glycol, poloxamer 407, polyethylene glycol 400, polysorbate 40, purified water, and tromethamine

Distributed by: Almirall, LLC

Exton, PA 19341

© 2018 Almirall. All rights reserved.

All trademarks are the property of their respective owners.

For more information, call 1-800-678-1605 or go to www.tazorac.com

This Patient Information has been approved by the U.S. Food and Drug Administration

Revised: April/2018

71722US17